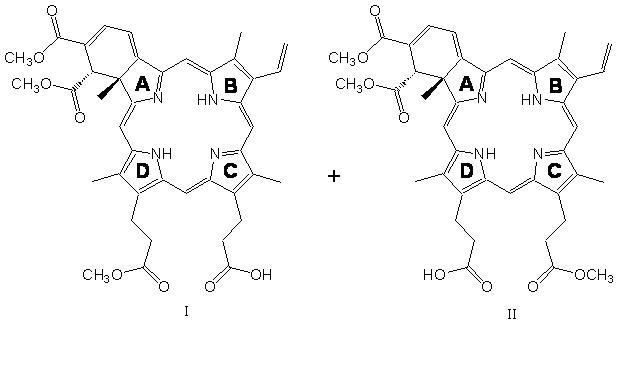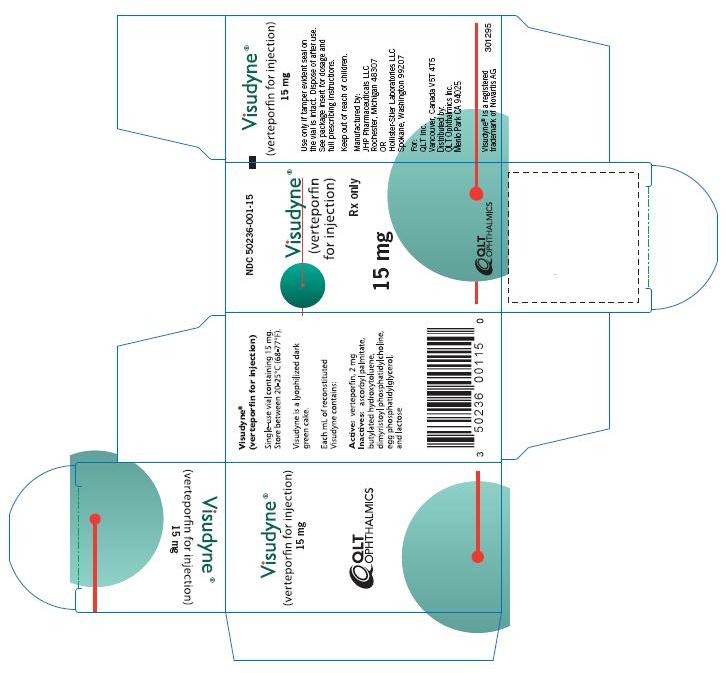 DRUG LABEL: Visudyne
NDC: 50236-001 | Form: INJECTION, POWDER, LYOPHILIZED, FOR SOLUTION
Manufacturer: QLT Ophthalmics, Inc.
Category: prescription | Type: HUMAN PRESCRIPTION DRUG LABEL
Date: 20100407

ACTIVE INGREDIENTS: VERTEPORFIN 15 mg/1 1
INACTIVE INGREDIENTS: ASCORBYL PALMITATE; BUTYLATED HYDROXYTOLUENE; LACTOSE

VISUDYNE®
(VERTEPORFIN FOR INJECTION)

DESCRIPTION

Visudyne® (verteporfin for injection) is a light activated drug used in photodynamic therapy. The finished drug product is a lyophilized dark green cake. Verteporfin is a 1:1 mixture of two regioisomers (I and II), represented by the following structures:

The chemical names for the verteporfin regioisomers are:

9-methyl (I) and 13-methyl (II) trans-(±)-18-ethenyl-4,4a-dihydro-3,4-bis(methoxycarbonyl)-4a,8,14,19-tetramethyl-23H, 25H-benzo[b]porphine-9,13-dipropanoate

The molecular formula is C41H42N4O8 with a molecular weight of approximately 718.8.

Each mL of reconstituted VISUDYNE contains:

ACTIVE: Verteporfin, 2 mg

INACTIVES: ascorbyl palmitate, butylated hydroxytoluene, dimyristoyl phosphatidylcholine, egg phosphatidylglycerol and lactose

CLINICAL PHARMACOLOGY

Mechanism of Action

Visudyne® (verteporfin for injection) therapy is a two-stage process requiring administration of both verteporfin for injection and nonthermal red light.

Verteporfin is transported in the plasma primarily by lipoproteins. Once verteporfin is activated by light in the presence of oxygen, highly reactive, short-lived singlet oxygen and reactive oxygen radicals are generated. Light activation of verteporfin results in local damage to neovascular endothelium, resulting in vessel occlusion. Damaged endothelium is known to release procoagulant and vasoactive factors through the lipo-oxygenase (leukotriene) and cyclo-oxygenase (eicosanoids such as thromboxane) pathways, resulting in platelet aggregation, fibrin clot formation and vasoconstriction. Verteporfin appears to somewhat preferentially accumulate in neovasculature, including choroidal neovasculature. However, animal models indicate that the drug is also present in the retina. Therefore, there may be collateral damage to retinal structures following photoactivation including the retinal pigmented epithelium and outer nuclear layer of the retina. The temporary occlusion of choroidal neovascularization (CNV) following Visudyne therapy has been confirmed in humans by fluorescein angiography.

Pharmacokinetics

Following intravenous infusion, verteporfin exhibits a bi-exponential elimination with a terminal elimination half-life of approximately 5-6 hours. The extent of exposure and the maximal plasma concentration are proportional to the dose between 6 and 20 mg/m^2. At the intended dose, pharmacokinetic parameters are not significantly affected by gender.

Verteporfin is metabolized to a small extent to its diacid metabolite by liver and plasma esterases. NADPH-dependent liver enzyme systems (including the cytochrome P450 isozymes) do not appear to play a role in the metabolism of verteporfin. Elimination is by the fecal route, with less than 0.01% of the dose recovered in urine.

In a study of patients with mild hepatic insufficiency (defined as having two abnormal hepatic function tests at enrollment), AUC and Cmax were not significantly different from the control group; half-life, however, was significantly increased by approximately 20%.

Clinical Studies

Age-Related Macular Degeneration (AMD)

Two adequate and well-controlled, double-masked, placebo-controlled, randomized studies were conducted in patients with classic-containing subfoveal CNV secondary to age-related macular degeneration. A total of 609 patients (Visudyne 402, placebo 207) were enrolled in these two studies. During these studies, retreatment was allowed every 3 months if fluorescein angiograms showed any recurrence or persistence of leakage. The placebo control (sham treatment) consisted of intravenous administration of Dextrose 5% in Water, followed by light application identical to that used for Visudyne therapy.

The difference between treatment groups statistically favored Visudyne at the 1-year and 2-year analyses for visual acuity endpoints.

The subgroup of patients with predominantly classic CNV lesions was more likely to exhibit a treatment benefit (N=242; Visudyne 159, placebo 83). Predominantly classic CNV lesions were defined as those in which the classic component comprised 50% or more of the area of the entire lesion. For the primary efficacy endpoint (percentage of patients who lost <3 lines of visual acuity), these patients showed a difference of approximately 28% between treatment groups at both Months 12 and 24 (67% for Visudyne patients compared to 40% for placebo patients, at Month 12; and 59% for Visudyne patients compared to 31% for placebo patients, at Month 24). Severe vision loss (≥6 lines of visual acuity from baseline) was experienced by 12% of Visudyne-treated patients compared to 34% of placebo-treated patients at Month 12, and by 15% of Visudyne-treated patients compared to 36% of placebo-treated patients at Month 24.

Patients with predominantly classic CNV lesions that did not contain occult CNV exhibited the greatest benefit (N=134; Visudyne 90, placebo 44). At 1 year, these patients demonstrated a 49% difference between treatment groups when assessed by the <3 lines-lost definition (77% vs. 27%).

Older patients (≥75 years), patients with dark irides, patients with occult lesions or patients with less than 50% classic CNV were less likely to benefit from Visudyne therapy.

The safety and efficacy of Visudyne beyond 2 years have not been demonstrated.

Based on the TAP extension study, the average number of treatments per year were 3.5 in the first year after diagnosis, 2.4 in the second, 1.3 in the third, 0.4 in the fourth and 0.1 in the fifth year.

Pathologic Myopia

One adequate and well-controlled, double-masked, placebo-controlled, randomized study was conducted in patients with subfoveal CNV secondary to pathologic myopia. A total of 120 patients (Visudyne 81, placebo 39) were enrolled in the study. The treatment dosing and retreatments were the same as in the AMD studies. The difference between treatment groups statistically favored Visudyne at the 1-year analysis but not at the 2-year analysis for visual acuity endpoints. For the primary efficacy endpoint (percentage of patients who lost <3 lines of visual acuity), patients at the 1-year timepoint showed a difference of approximately 19% between treatment groups (86% for Visudyne patients compared to 67% for placebo patients). However, by the 2-year timepoint, the effect was no longer statistically significant (79% for Visudyne patients compared to 72% for placebo patients).

Based on the VIP-PM extension study in pathologic myopia, the average number of treatments per year were 3.5 in the first year after diagnosis, 1.8 in the second, 0.4 in the third, 0.2 in the fourth and 0.1 in the fifth.

Presumed Ocular Histoplasmosis

One open-label study was conducted in patients with subfoveal CNV secondary to presumed ocular histoplasmosis. A total of 26 patients were treated with Visudyne in the study. The treatment dosing and retreatments for Visudyne were the same as in the AMD studies. Visudyne-treated patients compare favorably with historical control data demonstrating a reduction in the number of episodes of severe visual acuity loss (>6 lines of loss).

Based on the VOH extension study in presumed ocular histoplasmosis, the average number of treatments per year were 2.9 in the first year after diagnosis, 1.2 in the second, 0.2 in the third and 0.1 in the fourth.

INDICATIONS AND USAGE

Visudyne® (verteporfin for injection) therapy is indicated for the treatment of patients with predominantly classic subfoveal choroidal neovascularization due to age-related macular degeneration, pathologic myopia or presumed ocular histoplasmosis.

There is insufficient evidence to indicate Visudyne for the treatment of predominantly occult subfoveal choroidal neovascularization.

CONTRAINDICATIONS

Visudyne® (verteporfin for injection) is contraindicated for patients with porphyria or a known hypersensitivity to any component of this preparation.

WARNINGS

Following injection with Visudyne® (verteporfin for injection), care should be taken to avoid exposure of skin or eyes to direct sunlight or bright indoor light for 5 days. In the event of extravasation during infusion, the extravasation area must be thoroughly protected from direct light until the swelling and discoloration have faded in order to prevent the occurrence of a local burn which could be severe. If emergency surgery is necessary within 48 hours after treatment, as much of the internal tissue as possible should be protected from intense light.

Patients who experience severe decrease of vision of ≥4 lines within 1 week after treatment should not be retreated, at least until their vision completely recovers to pretreatment levels and the potential benefits and risks of subsequent treatment are carefully considered by the treating physician.

Use of incompatible lasers that do not provide the required characteristics of light for the photoactivation of Visudyne could result in incomplete treatment due to partial photoactivation of Visudyne , overtreatment due to overactivation of Visudyne , or damage to surrounding normal tissue.

PRECAUTIONS

General

Standard precautions should be taken during infusion of Visudyne® (verteporfin for injection) to avoid extravasation. Examples of standard precautions include, but are not limited to:

- A free-flowing intravenous (IV) line should be established before starting Visudyne infusion and the line should be carefully monitored.
- Due to the possible fragility of vein walls of some elderly patients, it is strongly recommended that the largest arm vein possible, preferably antecutibal, be used for injection.
- Small veins in the back of the hand should be avoided.

Extravasation of Visudyne, especially if the affected area is exposed to light, can cause severe pain, inflammation, swelling or discoloration at the injection site.

If extravasation does occur, the infusion should be stopped immediately. The extravasation area must be thoroughly protected from direct light until swelling and discoloration have faded in order to prevent the occurrence of a local burn, which could be severe. Cold compresses should be applied to the injection site. (see Warnings). Oral medications for pain relief may be administered.

Visudyne therapy should be considered carefully in patients with moderate to severe hepatic impairment or biliary obstruction since there is no clinical experience with verteporfin in such patients.

There is no clinical data related to the use of Visudyne in anesthetized patients. At a >10-fold higher dose given by bolus injection to sedated or anesthetized pigs, verteporfin caused severe hemodynamic effects, including death, probably as a result of complement activation. These effects were diminished or abolished by pretreatment with antihistamine and they were not seen in conscious nonsedated pigs. VISUDYNE resulted in a concentration-dependent increase in complement activation in human blood in vitro. At 10 µg/mL (approximately 5 times the expected plasma concentration in human patients), there was mild to moderate complement activation. At ≥100 µg/mL, there was significant complement activation. Signs (chest pain, syncope, dyspnea, and flushing) consistent with complement activation have been observed in <1% of patients administered Visudyne. Patients should be supervised during Visudyne infusion.

Information for Patients

Patients who receive Visudyne will become temporarily photosensitive after the infusion. Patients should wear a wristband to remind them to avoid direct sunlight for 5 days. During that period, patients should avoid exposure of unprotected skin, eyes or other body organs to direct sunlight or bright indoor light. Sources of bright light include, but are not limited to, tanning salons, bright halogen lighting and high power lighting used in surgical operating rooms or dental offices. Prolonged exposure to light from light-emitting medical devices such as pulse oximeters should also be avoided for 5 days following Visudyne administration.

If treated patients must go outdoors in daylight during the first 5 days after treatment, they should protect all parts of their skin and their eyes by wearing protective clothing and dark sunglasses. UV sunscreens are not effective in protecting against photosensitivity reactions because photoactivation of the residual drug in the skin can be caused by visible light.

Patients should not stay in the dark and should be encouraged to expose their skin to ambient indoor light, as it will help inactivate the drug in the skin through a process called photobleaching.

Following Visudyne treatment, patients may develop visual disturbances such as abnormal vision, vision decrease, or visual field defects that may interfere with their ability to drive or use machines. Patients should not drive or use machines as long as these symptoms persist.

Drug Interactions

Drug interaction studies in humans have not been conducted with Visudyne.

Verteporfin is rapidly eliminated by the liver, mainly as unchanged drug. Metabolism is limited and occurs by liver and plasma esterases. Microsomal cytochrome P450 does not appear to play a role in verteporfin metabolism.

Based on the mechanism of action of verteporfin, many drugs used concomitantly could influence the effect of Visudyne therapy. Possible examples include the following:

Calcium channel blockers, polymyxin B or radiation therapy could enhance the rate of Visudyne uptake by the vascular endothelium. Other photosensitizing agents (e.g., tetracyclines, sulfonamides, phenothiazines, sulfonylurea hypoglycemic agents, thiazide diuretics and griseofulvin) could increase the potential for skin photosensitivity reactions. Compounds that quench active oxygen species or scavenge radicals, such as dimethyl sulfoxide, β-carotene, ethanol, formate and mannitol, would be expected to decrease Visudyne activity. Drugs that decrease clotting, vasoconstriction or platelet aggregation, e.g., thromboxane A2 inhibitors, could also decrease the efficacy of Visudyne therapy.

Carcinogenesis, Mutagenesis, Impairment of Fertility

No studies have been conducted to evaluate the carcinogenic potential of verteporfin.

Photodynamic therapy (PDT) as a class has been reported to result in DNA damage including DNA strand breaks, alkali-labile sites, DNA degradation, and DNA-protein cross links which may result in chromosomal aberrations, sister chromatid exchanges (SCE), and mutations. In addition, other photodynamic therapeutic agents have been shown to increase the incidence of SCE in Chinese hamster ovary (CHO) cells irradiated with visible light and in Chinese hamster lung fibroblasts irradiated with near UV light, increase mutations and DNA-protein cross-linking in mouse L5178 cells, and increase DNA-strand breaks in malignant human cervical carcinoma cells, but not in normal cells. Verteporfin was not evaluated in these latter systems. It is not known how the potential for DNA damage with PDT agents translates into human risk.

No effect on male or female fertility has been observed in rats following intravenous administration of verteporfin for injection up to 10 mg/kg/day (approximately 60- and 40-fold human exposure at 6 mg/m^2 based on AUCinf in male and female rats, respectively).

Pregnancy

Teratogenic Effects: Pregnancy Category C

Rat fetuses of dams administered verteporfin for injection intravenously at ≥10 mg/kg/day during organogenesis (approximately 40-fold human exposure at 6 mg/m^2 based on AUCinf in female rats) exhibited an increase in the incidence of anophthalmia/microphthalmia. Rat fetuses of dams administered 25 mg/kg/day (approximately 125 fold the human exposure at 6 mg/m^2 based on AUCinf in female rats) had an increased incidence of wavy ribs and anophthalmia/microphthalmia.

In pregnant rabbits, a decrease in body weight gain and food consumption was observed in animals that received verteporfin for injection intravenously at ≥10 mg/kg/day during organogenesis. The no observed adverse effect level (NOAEL) for maternal toxicity was 3 mg/kg/day (approximately 7-fold human exposure at 6 mg/m^2 based on body surface area). There were no teratogenic effects observed in rabbits at doses up to 10 mg/kg/day.

There are no adequate and well-controlled studies in pregnant women. Visudyne should be used during pregnancy only if the benefit justifies the potential risk to the fetus.

Nursing Mothers

Verteporfin and its diacid metabolite have been found in the breast milk of one woman after a 6 mg/m^2 infusion. The verteporfin breast milk levels were up to 66% of the corresponding plasma levels and declined below the limit of quantification (2 ng/mL) within 24 hours. The diacid metabolite had lower peak concentrations but persisted up to at least 48 hours.

Because of the potential for serious adverse reactions in nursing infants from Visudyne, a decision should be made whether to discontinue nursing or postpone treatment, taking into account the importance of the drug to the mother.

Pediatric Use

Safety and effectiveness in pediatric patients have not been established.

Geriatric Use

Approximately 90% of the patients treated with Visudyne in the clinical efficacy trials were over the age of 65. A reduced treatment effect was seen with increasing age.

ADVERSE REACTIONS

Severe chest pain, vasovagal and hypersensitivity reactions have been reported. Vasovagal and hypersensitivity reactions on rare occasions can be severe. These reactions may include syncope, sweating, dizziness, rash, dyspnea, flushing and changes in blood pressure and heart rate. General symptoms can include headache, malaise, urticaria, and pruritus.

The most frequently reported adverse events to Visudyne® (verteporfin for injection) are injection site reactions (including pain, edema, inflammation, extravasation, rashes, hemorrhage and discoloration) and visual disturbances (including blurred vision, flashes of light, decreased visual acuity and visual field defects, including scotoma). These events occurred in approximately 10%-30% of patients. The following events, listed by Body System, were reported more frequently with Visudyne therapy than with placebo therapy and occurred in 1%-10% of patients:

Ocular Treatment Site: Blepharitis, cataracts, conjunctivitis/conjunctival injection, dry eyes, ocular itching, severe vision decrease with or without subretinal/retinal or vitreous hemorrhage

Body as a Whole: Asthenia, fever, flu syndrome, infusion related pain primarily presenting as back pain, photosensitivity reactions

Cardiovascular: Atrial fibrillation, hypertension, peripheral vascular disorder, varicose veins

Dermatologic: Eczema

Digestive: Constipation, gastrointestinal cancers, nausea

Hemic and Lymphatic: Anemia, white blood cell count decreased, white blood cell count increased

Hepatic: Elevated liver function tests

Metabolic/Nutritional: Albuminuria, creatinine increased

Musculoskeletal: Arthralgia, arthrosis, myasthenia

Nervous System: Hypesthesia, sleep disorder, vertigo

Respiratory: Cough, pharyngitis, pneumonia

Special Senses: Cataracts, decreased hearing, diplopia, lacrimation disorder

Urogenital: Prostatic disorder

Severe vision decrease, equivalent of ≥4 lines, within 7 days after treatment has been reported in 1%-5% of patients. Partial recovery of vision was observed in some patients. Photosensitivity reactions usually occurred in the form of skin sunburn following exposure to sunlight. The higher incidence of back pain in the Visudyne group occurred primarily during infusion.

The following adverse events have occurred either at low incidence (<1%) during clinical trials or have been reported during the use of Visudyne in clinical practice where these events were reported voluntarily from a population of unknown size and frequency of occurrence cannot be determined precisely. They have been chosen for inclusion based on factors such as seriousness, frequency of reporting, possible causal connection to Visudyne, or a combination of these factors:

Ocular Treatment Site: Retinal detachment (nonrhegmatogenous), retinal or choroidal vessel nonperfusion, retinal pigment epithelial tear

Non-ocular Events: Chest pain and other musculoskeletal pain during infusion

OVERDOSAGE

Overdose of drug and/or light in the treated eye may result in nonperfusion of normal retinal vessels with the possibility of severe decrease in vision that could be permanent. An overdose of drug will also result in the prolongation of the period during which the patient remains photosensitive to bright light. In such cases, it is recommended to extend the photosensitivity precautions for a time proportional to the overdose.

DOSAGE AND ADMINISTRATION

A course of Visudyne® (verteporfin for injection) therapy is a two-step process requiring administration of both drug and light.

The first step is the intravenous infusion of Visudyne. The second step is the activation of Visudyne with light from a nonthermal diode laser.

The physician should reevaluate the patient every 3 months and if choroidal neovascular leakage is detected on fluorescein angiography, therapy should be repeated.

Lesion Size Determination

The greatest linear dimension (GLD) of the lesion is estimated by fluorescein angiography and color fundus photography. All classic and occult CNV, blood and/or blocked fluorescence, and any serous detachments of the retinal pigment epithelium should be included for this measurement. Fundus cameras with magnification within the range of 2.4-2.6X are recommended. The GLD of the lesion on the fluorescein angiogram must be corrected for the magnification of the fundus camera to obtain the GLD of the lesion on the retina.

Spot Size Determination

The treatment spot size should be 1000 microns larger than the GLD of the lesion on the retina to allow a 500 micron border, ensuring full coverage of the lesion. The maximum spot size used in the clinical trials was 6400 microns.

The nasal edge of the treatment spot must be positioned at least 200 microns from the temporal edge of the optic disc, even if this will result in lack of photoactivation of CNV within 200 microns of the optic nerve.

Visudyne® Administration

Reconstitute each vial of Visudyne with 7 mL of sterile Water for Injection to provide 7.5 mL containing 2 mg/mL. Reconstituted Visudyne must be protected from light and used within 4 hours. It is recommended that reconstituted Visudyne be inspected visually for particulate matter and discoloration prior to administration. Reconstituted Visudyne is an opaque dark green solution. Visudyne may precipitate in saline solutions. Do not use normal saline or other parenteral solutions, except 5% Dextrose for Injection, for dilution of the reconstituted Visudyne. Do not mix Visudyne in the same solution with other drugs.

The volume of reconstituted Visudyne required to achieve the desired dose of 6 mg/m^2 body surface area is withdrawn from the vial and diluted with 5% Dextrose for Injection to a total infusion volume of 30 mL. After dilution, protect from light and use within a maximum of 4 hours. The full infusion volume is administered intravenously over 10 minutes at a rate of 3 mL/minute, using an appropriate syringe pump and in-line filter. The clinical studies were conducted using a standard infusion line filter of 1.2 microns.

Precautions should be taken to prevent extravasation at the injection site. If extravasation occurs, protect the site from light (See PRECAUTIONS).

Light Administration

Initiate 689 nm wavelength laser light delivery to the patient 15 minutes after the start of the 10-minute infusion with Visudyne.

Photoactivation of Visudyne is controlled by the total light dose delivered. In the treatment of choroidal neovascularization, the recommended light dose is 50 J/cm^2 of neovascular lesion administered at an intensity of 600 mW/cm^2. This dose is administered over 83 seconds.

Light dose, light intensity, ophthalmic lens magnification factor and zoom lens setting are important parameters for the appropriate delivery of light to the predetermined treatment spot. Follow the laser system manuals for procedure set up and operation.

The laser system must deliver a stable power output at a wavelength of 689±3 nm. Light is delivered to the retina as a single circular spot via a fiber optic and a slit lamp, using a suitable ophthalmic magnification lens.

The following laser systems have been tested for compatibility with Visudyne and are approved for delivery of a stable power output at a wavelength of 689±3 nm:

Coherent Opal Photoactivator laser console and modified Coherent LaserLink adapter, manufactured by Lumenis, Inc., 2400 Condensa Street, Santa Clara, CA 95051-0901,

Zeiss VISULAS 690s laser and VISULINK® PDT adapter manufactured by Carl Zeiss Meditec Inc., 5160 Hacienda Drive, Dublin, CA 94568,

Ceralas™ I laser system and Ceralink™ Slit Lamp Adapter manufactured by Biolitec Inc., 515 Shaker Road, East Longmeadow, MA 01028,

Quantel Activis laser console and the ZSL30 ACT™, ZSL120 ACT™ and HSBMBQ ACT™ slit lamp adapters distributed by Quantel Medical, 601 Haggerty Lane, Bozeman, MT 59715.

Concurrent Bilateral Treatment

The controlled trials only allowed treatment of one eye per patient. In patients who present with eligible lesions in both eyes, physicians should evaluate the potential benefits and risks of treating both eyes concurrently. If the patient has already received previous Visudyne therapy in one eye with an acceptable safety profile, both eyes can be treated concurrently after a single administration of Visudyne. The more aggressive lesion should be treated first, at 15 minutes after the start of infusion. Immediately at the end of light application to the first eye, the laser settings should be adjusted to introduce the treatment parameters for the second eye, with the same light dose and intensity as for the first eye, starting no later than 20 minutes from the start of infusion.

In patients who present for the first time with eligible lesions in both eyes without prior Visudyne therapy, it is prudent to treat only one eye (the most aggressive lesion) at the first course. One week after the first course, if no significant safety issues are identified, the second eye can be treated using the same treatment regimen after a second Visudyne infusion. Approximately 3 months later, both eyes can be evaluated and concurrent treatment following a new Visudyne infusion can be started if both lesions still show evidence of leakage.

HOW SUPPLIED

Visudyne (verteporfin for injection) is supplied in a single use glass vial with a gray bromobutyl stopper and aluminum flip-off cap. It contains a lyophilized dark green cake with 15 mg verteporfin. The product is intended for intravenous injection only.

Spills and Disposal

Spills of Visudyne should be wiped up with a damp cloth. Skin and eye contact should be avoided due to the potential for photosensitivity reactions upon exposure to light. Use of rubber gloves and eye protection is recommended. All materials should be disposed of properly.

Accidental Exposure

Because of the potential to induce photosensitivity reactions, it is important to avoid contact with the eyes and skin during preparation and administration of Visudyne. Any exposed person must be protected from bright light (See WARNINGS).

NDC 50236-001-15

Store Visudyne between 20°C and 25°C (68°F-77°F).

REV: JANUARY 2010

301293 CC# 100020

QLT Inc.

Vancouver, Canada V5T 4T5

Distributed by:

QLT Ophthalmics Inc.

Menlo Park CA 94025

Visudyne® is a registered trademark of Novartis AG

PRINCIPAL DISPLAY PANEL

Visudyne Carton